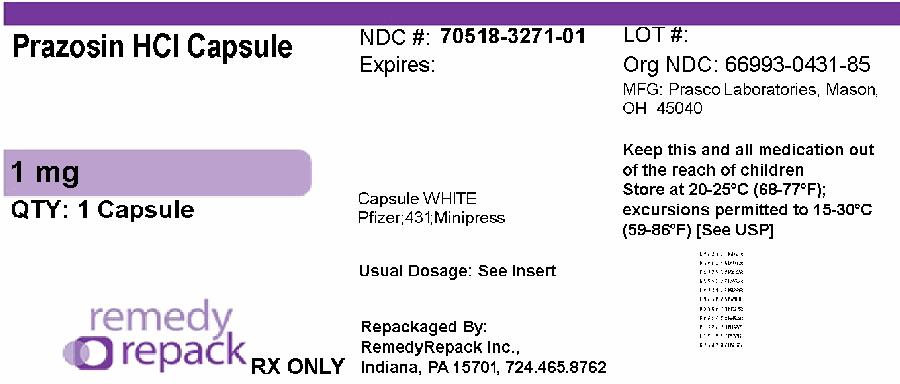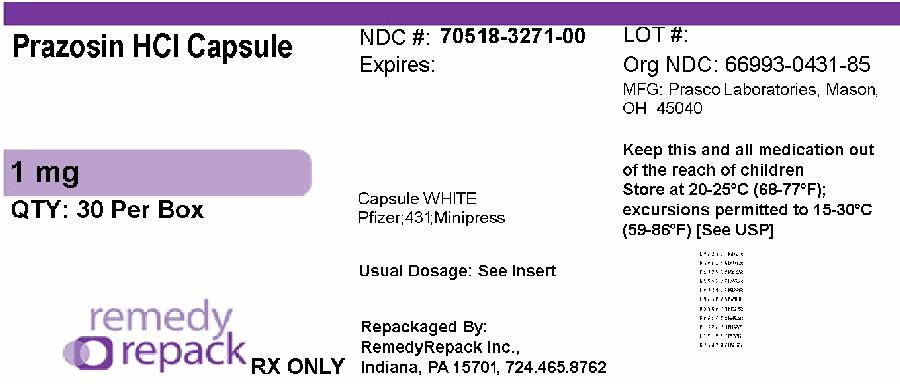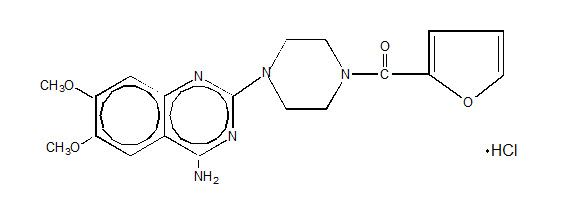 DRUG LABEL: Prazosin Hydrochloride
NDC: 70518-3271 | Form: CAPSULE
Manufacturer: REMEDYREPACK INC.
Category: prescription | Type: HUMAN PRESCRIPTION DRUG LABEL
Date: 20250718

ACTIVE INGREDIENTS: PRAZOSIN HYDROCHLORIDE 1 mg/1 1
INACTIVE INGREDIENTS: FD&C BLUE NO. 1; FD&C RED NO. 3; D&C RED NO. 28; FD&C RED NO. 40; MAGNESIUM STEARATE; SODIUM LAURYL SULFATE; SUCROSE

Prazosin Hydrochloride Capsules

For Oral Use

DESCRIPTION

Prazosin hydrochloride, a quinazoline derivative, is the first of a new chemical class of antihypertensives. It is the hydrochloride salt of 1-(4-amino-6,7-dimethoxy- 2-quinazolinyl)-4-(2-furoyl) piperazine and its structural formula is:

It is a white, crystalline substance, slightly soluble in water and isotonic saline, and has a molecular weight of 419.87. Each 1 mg capsule of prazosin hydrochloride for oral use contains drug equivalent to 1 mg free base.

Inert ingredients in the formulations are: hard gelatin capsules (which may contain Blue 1, Red 3, Red 28, Red 40, and other inert ingredients); magnesium stearate; sodium lauryl sulfate; starch; sucrose.

CLINICAL PHARMACOLOGY

The exact mechanism of the hypotensive action of prazosin is unknown. Prazosin causes a decrease in total peripheral resistance and was originally thought to have a direct relaxant action on vascular smooth muscle. Recent animal studies, however, have suggested that the vasodilator effect of prazosin is also related to blockade of postsynaptic alpha-adrenoceptors. The results of dog forelimb experiments demonstrate that the peripheral vasodilator effect of prazosin is confined mainly to the level of the resistance vessels (arterioles). Unlike conventional alpha-blockers, the antihypertensive action of prazosin is usually not accompanied by a reflex tachycardia. Tolerance has not been observed to develop in long term therapy.

Hemodynamic studies have been carried out in man following acute single dose administration and during the course of long term maintenance therapy. The results confirm that the therapeutic effect is a fall in blood pressure unaccompanied by a clinically significant change in cardiac output, heart rate, renal blood flow and glomerular filtration rate. There is no measurable negative chronotropic effect.

In clinical studies to date, prazosin hydrochloride has not increased plasma renin activity.

In man, blood pressure is lowered in both the supine and standing positions. This effect is most pronounced on the diastolic blood pressure.

Following oral administration, human plasma concentrations reach a peak at about three hours with a plasma half-life of two to three hours. The drug is highly bound to plasma protein. Bioavailability studies have demonstrated that the total absorption relative to the drug in a 20% alcoholic solution is 90%, resulting in peak levels approximately 65% of that of the drug in solution. Animal studies indicate that prazosin hydrochloride is extensively metabolized, primarily by demethylation and conjugation, and excreted mainly via bile and feces. Less extensive human studies suggest similar metabolism and excretion in man.

In clinical studies in which lipid profiles were followed, there were generally no adverse changes noted between pre- and post-treatment lipid levels.

INDICATIONS AND USAGE

Prazosin hydrochloride capsules are indicated for the treatment of hypertension, to lower blood pressure. Lowering blood pressure reduces the risk of fatal and nonfatal cardiovascular events, primarily strokes and myocardial infarctions. These benefits have been seen in controlled trials of antihypertensive drugs from a wide variety of pharmacologic classes, including this drug.

Control of high blood pressure should be part of comprehensive cardiovascular risk management, including, as appropriate, lipid control, diabetes management, antithrombotic therapy, smoking cessation, exercise, and limited sodium intake. Many patients will require more than one drug to achieve blood pressure goals. For specific advice on goals and management, see published guidelines, such as those of the National High Blood Pressure Education Program's Joint National Committee on Prevention, Detection, Evaluation, and Treatment of High Blood Pressure (JNC).

Numerous antihypertensive drugs, from a variety of pharmacologic classes and with different mechanisms of action, have been shown in randomized controlled trials to reduce cardiovascular morbidity and mortality, and it can be concluded that it is blood pressure reduction, and not some other pharmacologic property of the drugs, that is largely responsible for those benefits. The largest and most consistent cardiovascular outcome benefit has been a reduction in the risk of stroke, but reductions in myocardial infarction and cardiovascular mortality also have been seen regularly.

Elevated systolic or diastolic pressure causes increased cardiovascular risk, and the absolute risk increase per mmHg is greater at higher blood pressures, so that even modest reductions of severe hypertension can provide substantial benefit. Relative risk reduction from blood pressure reduction is similar across populations with varying absolute risk, so the absolute benefit is greater in patients who are at higher risk independent of their hypertension (for example, patients with diabetes or hyperlipidemia), and such patients would be expected to benefit from more aggressive treatment to a lower blood pressure goal.

Some antihypertensive drugs have smaller blood pressure effects (as monotherapy) in black patients, and many antihypertensive drugs have additional approved indications and effects (e.g., on angina, heart failure, or diabetic kidney disease). These considerations may guide selection of therapy.

Prazosin hydrochloride capsules can be used alone or in combination with other antihypertensive drugs such as diuretics or beta-adrenergic blocking agents.

CONTRAINDICATIONS

Prazosin hydrochloride capsules are contraindicated in patients with known sensitivity to quinazolines, prazosin, or any of the inert ingredients.

WARNINGS

As with all alpha-blockers, prazosin hydrochloride capsules may cause syncope with sudden loss of consciousness. In most cases, this is believed to be due to an excessive postural hypotensive effect, although occasionally the syncopal episode has been preceded by a bout of severe tachycardia with heart rates of 120–160 beats per minute. Syncopal episodes have usually occurred within 30 to 90 minutes of the initial dose of the drug; occasionally, they have been reported in association with rapid dosage increases or the introduction of another antihypertensive drug into the regimen of a patient taking high doses of prazosin hydrochloride capsules. The incidence of syncopal episodes is approximately 1% in patients given an initial dose of 2 mg or greater. Clinical trials conducted during the investigational phase of this drug suggest that syncopal episodes can be minimized by limiting the initial dose of the drug to 1 mg, by subsequently increasing the dosage slowly, and by introducing any additional antihypertensive drugs into the patient's regimen with caution (see DOSAGE AND ADMINISTRATION). Hypotension may develop in patients given prazosin hydrochloride capsules who are also receiving a beta-blocker such as propranolol.

If syncope occurs, the patient should be placed in the recumbent position and treated supportively as necessary. This adverse effect is self-limiting and in most cases does not recur after the initial period of therapy or during subsequent dose titration.

Patients should always be started on the 1 mg capsules of prazosin hydrochloride. The 2 and 5 mg capsules are not indicated for initial therapy.

More common than loss of consciousness are the symptoms often associated with lowering of the blood pressure, namely, dizziness and lightheadedness. The patient should be cautioned about these possible adverse effects and advised what measures to take should they develop. The patient should also be cautioned to avoid situations where injury could result should syncope occur during the initiation of prazosin hydrochloride therapy.

Priapism

Prolonged erections and priapism have been reported with alpha-1 blockers including prazosin in post marketing experience. In the event of an erection that persists longer than 4 hours, seek immediate medical assistance. If priapism is not treated immediately, penile tissue damage and permanent loss of potency could result.

PRECAUTIONS

General

Intraoperative Floppy Iris Syndrome (IFIS) has been observed during cataract surgery in some patients treated with alpha-1 blockers. This variant of small pupil syndrome is characterized by the combination of a flaccid iris that billows in response to intraoperative irrigation currents, progressive intraoperative miosis despite preoperative dilation with standard mydriatic drugs, and potential prolapse of the iris toward the phacoemulsification incisions. The patient's ophthalmologist should be prepared for possible modifications to the surgical technique, such as the utilization of iris hooks, iris dilator rings, or viscoelastic substances. There does not appear to be a benefit of stopping alpha-1 blocker therapy prior to cataract surgery.

Information for Patients

Dizziness or drowsiness may occur after the first dose of this medicine. Avoid driving or performing hazardous tasks for the first 24 hours after taking this medicine or when the dose is increased. Dizziness, lightheadedness, or fainting may occur, especially when rising from a lying or sitting position. Getting up slowly may help lessen the problem. These effects may also occur if you drink alcohol, stand for long periods of time, exercise, or if the weather is hot. While taking prazosin hydrochloride capsules, be careful in the amount of alcohol you drink. Also, use extra care during exercise or hot weather, or if standing for long periods. Check with your physician if you have any questions.

Repackaged By / Distributed By: RemedyRepack Inc.

625 Kolter Drive, Indiana, PA 15701

(724) 465-8762

Drug Interactions

Prazosin hydrochloride capsules have been administered without any adverse drug interaction in limited clinical experience to date with the following: (1) cardiac glycosides– digitalis and digoxin; (2) hypoglycemics–insulin, chlorpropamide, phenformin, tolazamide, and tolbutamide; (3) tranquilizers and sedatives–chlordiazepoxide, diazepam, and phenobarbital; (4) antigout–allopurinol, colchicine, and probenecid; (5) antiarrhythmics–procainamide, propranolol (see WARNINGShowever), and quinidine; and (6) analgesics, antipyretics and anti-inflammatories–propoxyphene, aspirin, indomethacin, and phenylbutazone.

Addition of a diuretic or other antihypertensive agent to prazosin hydrochloride capsules has been shown to cause an additive hypotensive effect. This effect can be minimized by reducing the prazosin hydrochloride dose to 1 to 2 mg three times a day, by introducing additional antihypertensive drugs cautiously, and then by retitrating prazosin hydrochloride based on clinical response.

Concomitant administration of prazosin hydrochloride capsules with a phosphodiesterase-5 (PDE-5) inhibitor can result in additive blood pressure lowering effects and symptomatic hypotension (see DOSAGE AND ADMINISTRATION).

Drug/Laboratory Test Interactions

In a study on five patients given from 12 to 24 mg of prazosin per day for 10 to 14 days, there was an average increase of 42% in the urinary metabolite of norepinephrine and an average increase in urinary VMA of 17%. Therefore, false positive results may occur in screening tests for pheochromocytoma in patients who are being treated with prazosin. If an elevated VMA is found, prazosin should be discontinued and the patient retested after a month.

Laboratory Tests

In clinical studies in which lipid profiles were followed, there were generally no adverse changes noted between pre- and post-treatment lipid levels.

Carcinogenesis, Mutagenesis, Impairment of Fertility

No carcinogenic potential was demonstrated in an 18 month study in rats with prazosin hydrochloride at dose levels more than 225 times the usual maximum recommended human dose of 20 mg per day. Prazosin hydrochloride was not mutagenic in in vivogenetic toxicology studies. In a fertility and general reproductive performance study in rats, both males and females, treated with 75 mg/kg (225 times the usual maximum recommended human dose), demonstrated decreased fertility, while those treated with 25 mg/kg (75 times the usual maximum recommended human dose) did not.

In chronic studies (one year or more) of prazosin hydrochloride in rats and dogs, testicular changes consisting of atrophy and necrosis occurred at 25 mg/kg/day (75 times the usual maximum recommended human dose). No testicular changes were seen in rats or dogs at 10 mg/kg/day (30 times the usual maximum recommended human dose). In view of the testicular changes observed in animals, 105 patients on long term prazosin hydrochloride therapy were monitored for 17-ketosteroid excretion and no changes indicating a drug effect were observed. In addition, 27 males on prazosin hydrochloride for up to 51 months did not have changes in sperm morphology suggestive of drug effect.

Usage in Pregnancy

Prazosin hydrochloride has been shown to be associated with decreased litter size at birth, 1, 4, and 21 days of age in rats when given doses more than 225 times the usual maximum recommended human dose. No evidence of drug-related external, visceral, or skeletal fetal abnormalities were observed. No drug-related external, visceral, or skeletal abnormalities were observed in fetuses of pregnant rabbits and pregnant monkeys at doses more than 225 times and 12 times the usual maximum recommended human dose, respectively.

The use of prazosin and a beta-blocker for the control of severe hypertension in 44 pregnant women revealed no drug-related fetal abnormalities or adverse effects. Therapy with prazosin was continued for as long as 14 weeks.^1

Prazosin has also been used alone or in combination with other hypotensive agents in severe hypertension of pregnancy by other investigators. No fetal or neonatal abnormalities have been reported with the use of prazosin.^2

There are no adequate and well controlled studies which establish the safety of prazosin hydrochloride in pregnant women. Prazosin hydrochloride should be used during pregnancy only if the potential benefit justifies the potential risk to the mother and fetus.

Nursing Mothers

Prazosin hydrochloride has been shown to be excreted in small amounts in human milk. Caution should be exercised when prazosin hydrochloride is administered to a nursing woman.

Usage in Children

Safety and effectiveness in children have not been established.

ADVERSE REACTIONS

Clinical trials were conducted on more than 900 patients. During these trials and subsequent marketing experience, the most frequent reactions associated with prazosin hydrochloride therapy are: dizziness 10.3%, headache 7.8%, drowsiness 7.6%, lack of energy 6.9%, weakness 6.5%, palpitations 5.3%, and nausea 4.9%. In most instances, side effects have disappeared with continued therapy or have been tolerated with no decrease in dose of drug.

Less frequent adverse reactions which are reported to occur in 1–4% of patients are:

Gastrointestinal:vomiting, diarrhea, constipation.

Cardiovascular:edema, orthostatic hypotension, dyspnea, syncope.

Central Nervous System:vertigo, depression, nervousness.

Dermatologic:rash.

Genitourinary:urinary frequency.

EENT:blurred vision, reddened sclera, epistaxis, dry mouth, nasal congestion.

In addition, fewer than 1% of patients have reported the following (in some instances, exact causal relationships have not been established):

Gastrointestinal:abdominal discomfort and/or pain, liver function abnormalities, pancreatitis.

Cardiovascular:tachycardia.

Central Nervous System:paresthesia, hallucinations.

Dermatologic:pruritus, alopecia, lichen planus.

Genitourinary:incontinence, impotence, priapism.

EENT:tinnitus.

Other:diaphoresis, fever, positive ANA titer, arthralgia.

Single reports of pigmentary mottling and serous retinopathy, and a few reports of cataract development or disappearance have been reported. In these instances, the exact causal relationship has not been established because the baseline observations were frequently inadequate.

In more specific slit-lamp and funduscopic studies, which included adequate baseline examinations, no drug-related abnormal ophthalmological findings have been reported.

Literature reports exist associating prazosin hydrochloride therapy with a worsening of pre-existing narcolepsy. A causal relationship is uncertain in these cases.

In post-marketing experience, the following adverse events have been reported:

Autonomic Nervous System:flushing.

Body As A Whole:allergic reaction, asthenia, malaise, pain.

Cardiovascular, General:angina pectoris, hypotension.

Endocrine:gynecomastia.

Heart Rate/Rhythm:bradycardia.

Psychiatric:insomnia.

Skin/Appendages:urticaria.

Vascular (Extracardiac):vasculitis.

Vision:eye pain.

Special Senses:During cataract surgery, a variant of small pupil syndrome known as Intraoperative Floppy Iris Syndrome (IFIS) has been reported in association with alpha-1 blocker therapy (see PRECAUTIONS).

OVERDOSAGE

Accidental ingestion of at least 50 mg of prazosin hydrochloride in a two year old child resulted in profound drowsiness and depressed reflexes. No decrease in blood pressure was noted. Recovery was uneventful.

Should overdosage lead to hypotension, support of the cardiovascular system is of first importance. Restoration of blood pressure and normalization of heart rate may be accomplished by keeping the patient in the supine position. If this measure is inadequate, shock should first be treated with volume expanders. If necessary, vasopressors should then be used. Renal function should be monitored and supported as needed. Laboratory data indicate prazosin hydrochloride is not dialysable because it is protein bound.

DOSAGE AND ADMINISTRATION

The dose of prazosin hydrochloride capsules should be adjusted according to the patient's individual blood pressure response. The following is a guide to its administration:

Initial Dose

1 mg two or three times a day (see WARNINGS.)

Maintenance Dose

Dosage may be slowly increased to a total daily dose of 20 mg given in divided doses. The therapeutic dosages most commonly employed have ranged from 6 mg to 15 mg daily given in divided doses. Doses higher than 20 mg usually do not increase efficacy, however a few patients may benefit from further increases up to a daily dose of 40 mg given in divided doses. After initial titration some patients can be maintained adequately on a twice daily dosage regimen.

Use With Other Drugs

When adding a diuretic or other antihypertensive agent, the dose of prazosin hydrochloride capsules should be reduced to 1 mg or 2 mg three times a day and retitration then carried out.

Concomitant administration of prazosin hydrochloride capsules with a PDE-5 inhibitor can result in additive blood pressure lowering effects and symptomatic hypotension; therefore, PDE-5 inhibitor therapy should be initiated at the lowest dose in patients taking prazosin hydrochloride capsules.

HOW SUPPLIED

Prazosin hydrochloride 1 mg. capsule color: white, capsules code: 431

NDC: 70518-3271-00

NDC: 70518-3271-01

NDC: 70518-3271-02

PACKAGING: 30 in 1 BOX

PACKAGING: 1 in 1 POUCH

PACKAGING: 30 in 1 BLISTER PACK

Repackaged and Distributed By:

Remedy Repack, Inc.

625 Kolter Dr. Suite #4 Indiana, PA 1-724-465-8762

References

1. Lubbe, WF, and Hodge, JV: New Zealand Med J,94(691) 169–172, 1981.

2. Davey, DA, and Dommisse, J: S.A. Med J, Oct. 4, 1980 (551–556).

PACKAGE LABEL

DRUG: Prazosin Hydrochloride

GENERIC: prazosin hydrochloride

DOSAGE: CAPSULE

ADMINSTRATION: ORAL

NDC: 70518-3271-0

NDC: 70518-3271-1

NDC: 70518-3271-2

COLOR: white

SHAPE: CAPSULE

SCORE: No score

SIZE: 18 mm

IMPRINT: Pfizer;431;Minipress

PACKAGING: 1 in 1 POUCH

OUTER PACKAGING: 30 in 1 BOX

PACKAGING: 30 in 1 BLISTER PACK

ACTIVE INGREDIENT(S):

- PRAZOSIN HYDROCHLORIDE 1mg in 1

INACTIVE INGREDIENT(S):

- FD&C BLUE NO. 1
- FD&C RED NO. 3
- D&C RED NO. 28
- FD&C RED NO. 40
- MAGNESIUM STEARATE
- SODIUM LAURYL SULFATE
- SUCROSE